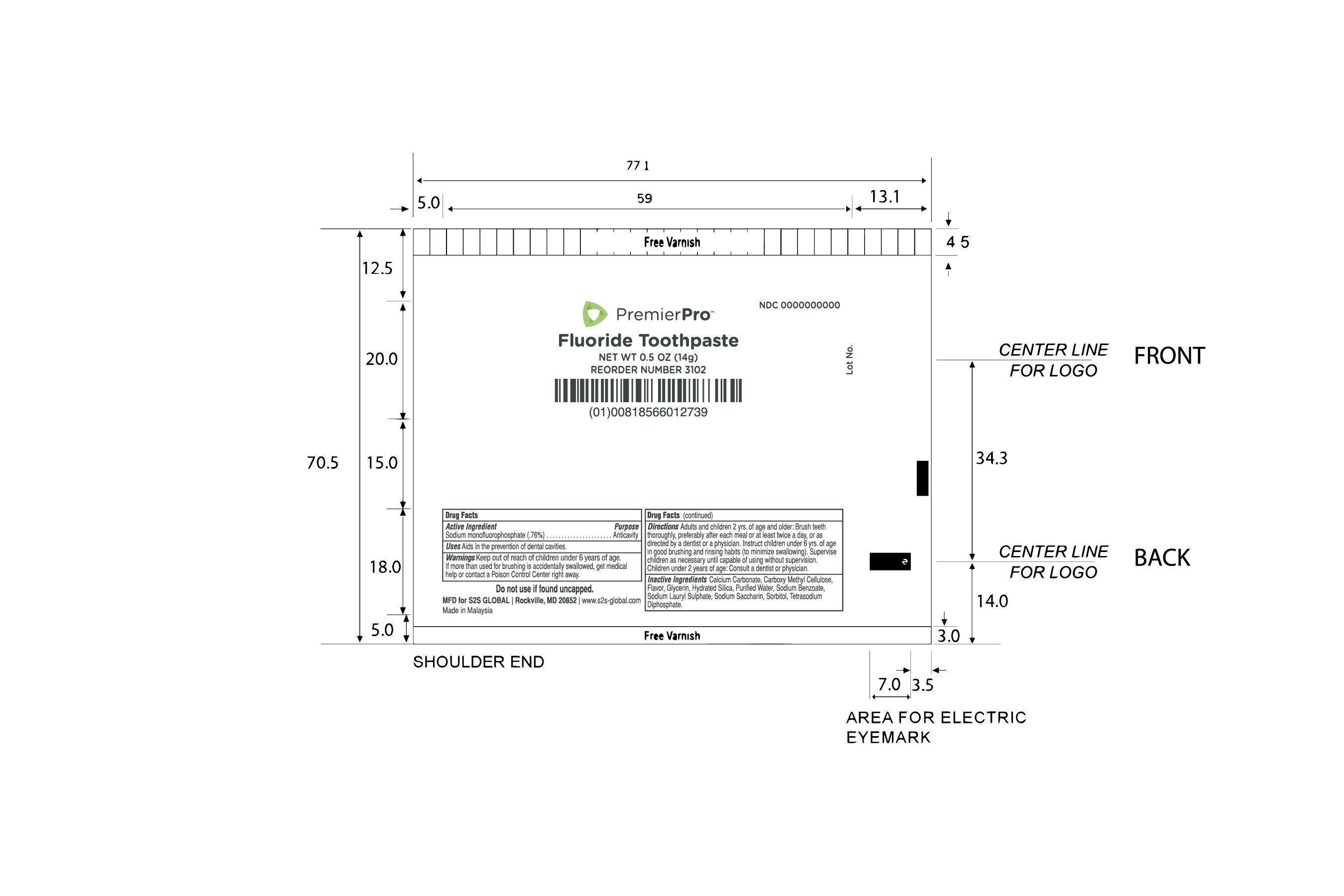 DRUG LABEL: PremierPro Fluoride Tooth
NDC: 69392-001 | Form: PASTE, DENTIFRICE
Manufacturer: SVS, LLC (DBA S2S Global)
Category: otc | Type: HUMAN OTC DRUG LABEL
Date: 20150119

ACTIVE INGREDIENTS: SODIUM MONOFLUOROPHOSPHATE 0.10 g/100 g
INACTIVE INGREDIENTS: WATER; SORBITOL; CALCIUM CARBONATE; CARBOXYMETHYLCELLULOSE SODIUM (0.7 CARBOXYMETHYL SUBSTITUTION PER SACCHARIDE; 100-200 MPA.S AT 1%); SODIUM LAURYL SULFATE; GLYCERIN; HYDRATED SILICA; SACCHARIN SODIUM; SODIUM BENZOATE; SODIUM PYROPHOSPHATE

Active Ingredient: Sodium Monofluorophosphate (0.76%)

Purpose: Anticavity

INDICATIONS AND USAGE

Uses: Aids in the prevention of dental cavities

WARNINGS

For external use only.

Keep out of reach of children under six years of age

ASK DOCTOR

If more than used for brushing is accidentally swallowed, get medical help or contact a poison control center right away

DOSAGE AND ADMINISTRATION

Adults and children of two years of age and older: Brush teeth thoroughly, perferrably after each meal or at least twice a day, or as directed by a dentist or a doctor. Instruct children under six years of age in good brushing and rinsing habit (to minimize swollowing). Supervise children as necessary until capable of using without supervision. Children under 2 years of age: consult a dentist or physician.

INACTIVE INGREDIENT

Calcium Carbonate, Carboxymethylcellulose Sodium, Flavour, Glycerin, Purified Water, Sodium Benzoate, Sodium Lauryl Sulfate, Hydrated Silica, Saccharin Sodium, Sorbitol, Tetrasodium Diphosphate.